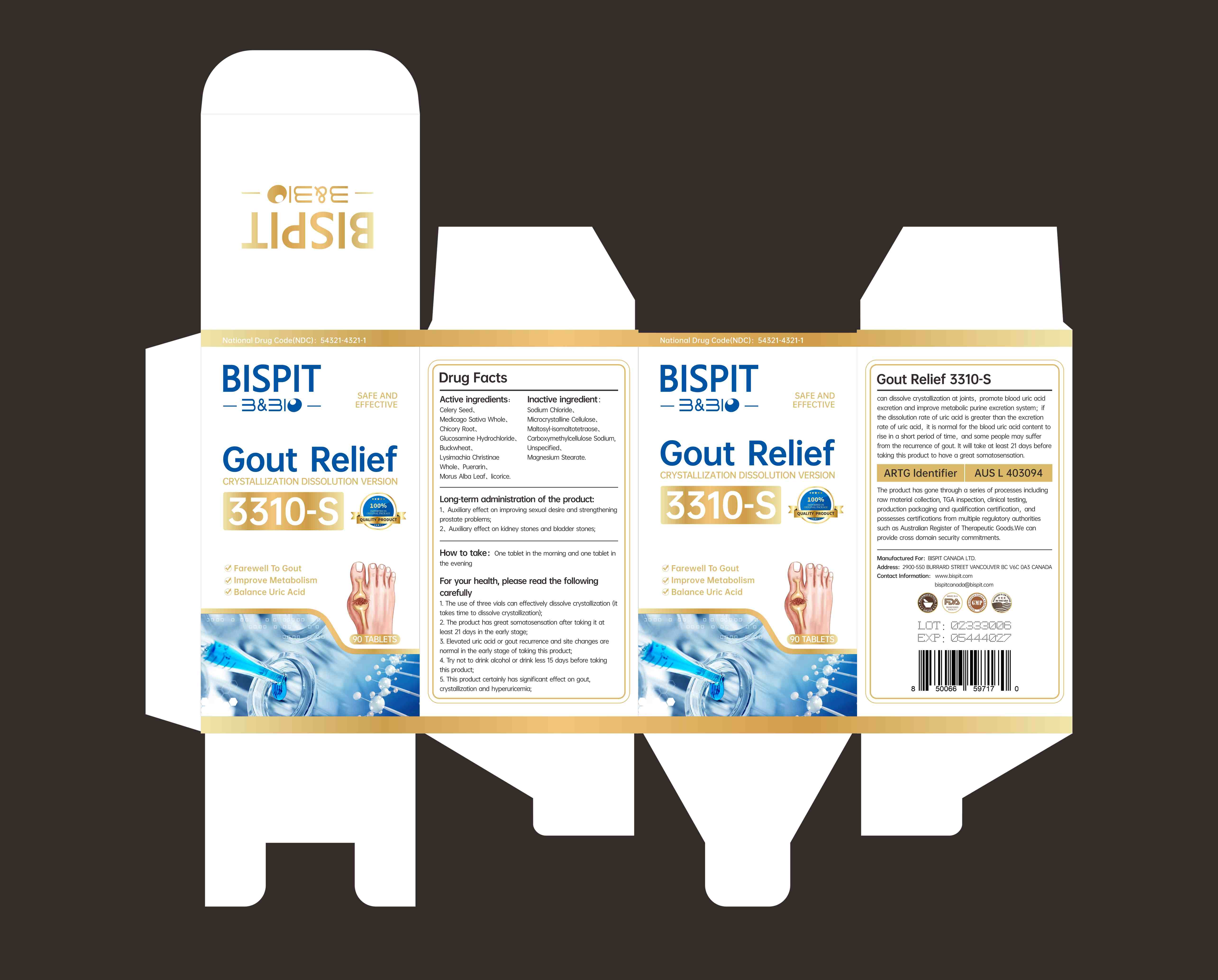 DRUG LABEL: Gout Relief 3310-S
NDC: 85631-001 | Form: CAPSULE
Manufacturer: Bispit Canada Ltd.
Category: homeopathic | Type: HUMAN OTC DRUG LABEL
Date: 20250505

ACTIVE INGREDIENTS: LYSIMACHIA CHRISTINAE WHOLE 65 mg/1.3 g; MEDICAGO SATIVA WHOLE 260 mg/1.3 g; PUERARIN 65 mg/1.3 g; SODIUM CHLORIDE 26 mg/1.3 g; CHICORY ROOT 230 mg/1.3 g; GLUCOSAMINE HYDROCHLORIDE 130 mg/1.3 g; BUCKWHEAT 90 mg/1.3 g; LICORICE 2.6 mg/1.3 g; CELERY SEED 260 mg/1.3 g; MORUS ALBA LEAF 39 mg/1.3 g
INACTIVE INGREDIENTS: CARBOXYMETHYLCELLULOSE SODIUM, UNSPECIFIED FORM; MAGNESIUM STEARATE; CELLULOSE, MICROCRYSTALLINE; MALTOSYL-ISOMALTOTETRAOSE

85631-001-01 Gout Relief 3310-S

ACTIVE INGREDIENT

CELERY SEED
MEDICAGO SATIVA WHOLE
CHICORY ROOT
GLUCOSAMINE HYDROCHLORIDE
BUCKWHEAT
LYSIMACHIA CHRISTINAE WHOLE
PUERARIN
MORUS ALBA LEAF
LICORICE
SODIUM CHLORIDE

PURPOSE

Farewell To Gout

lmprove Metabolism

Balance Uric Acid

Keep out of reach of children

DOSAGE AND ADMINISTRATION

2. The product has great somatosensation after taking it atleast 21 days in the earty stage;3. Elevated uric acid or gout recurrence and site changes arenoral in the earty stage of taking this product;

INDICATIONS AND USAGE

Long-term administration of the product:1、Auxiliary effect on improving sexual desire and strengtheningprostate problems;
2、Auxiliary effect on kidney stones and bladder stones;

WARNINGS

For your health, please read the followingcarefully
1. The use of three vials can effectivety dissolve crystallization (ittakes time to dissolve crystallization);2. The product has great somatosensation after taking it atleast 21 days in the early stage;3. Elevated uric acid or gout recurrence and site changes arenormal in the early stage of taking this product;4. Try not to drink alcohol or drink less 15 days before takingthis product;
5. This product certainly has significant effect on gout,crystallization and hyperuricemia;

Do not use if seal is broken.

Do not eat freshness packet enclosed.

Keep out of direct sunlight, high temperature, and humidity.

Store in a cool, dry place.

INACTIVE INGREDIENT

MICROCRYSTALLINE CELLULOSE
MALTOSYL-ISOMALTOTETRAOSE
CARBOXYMETHYLCELLULOSE SODIUM, UNSPECIFIED
MAGNESIUM STEARATE